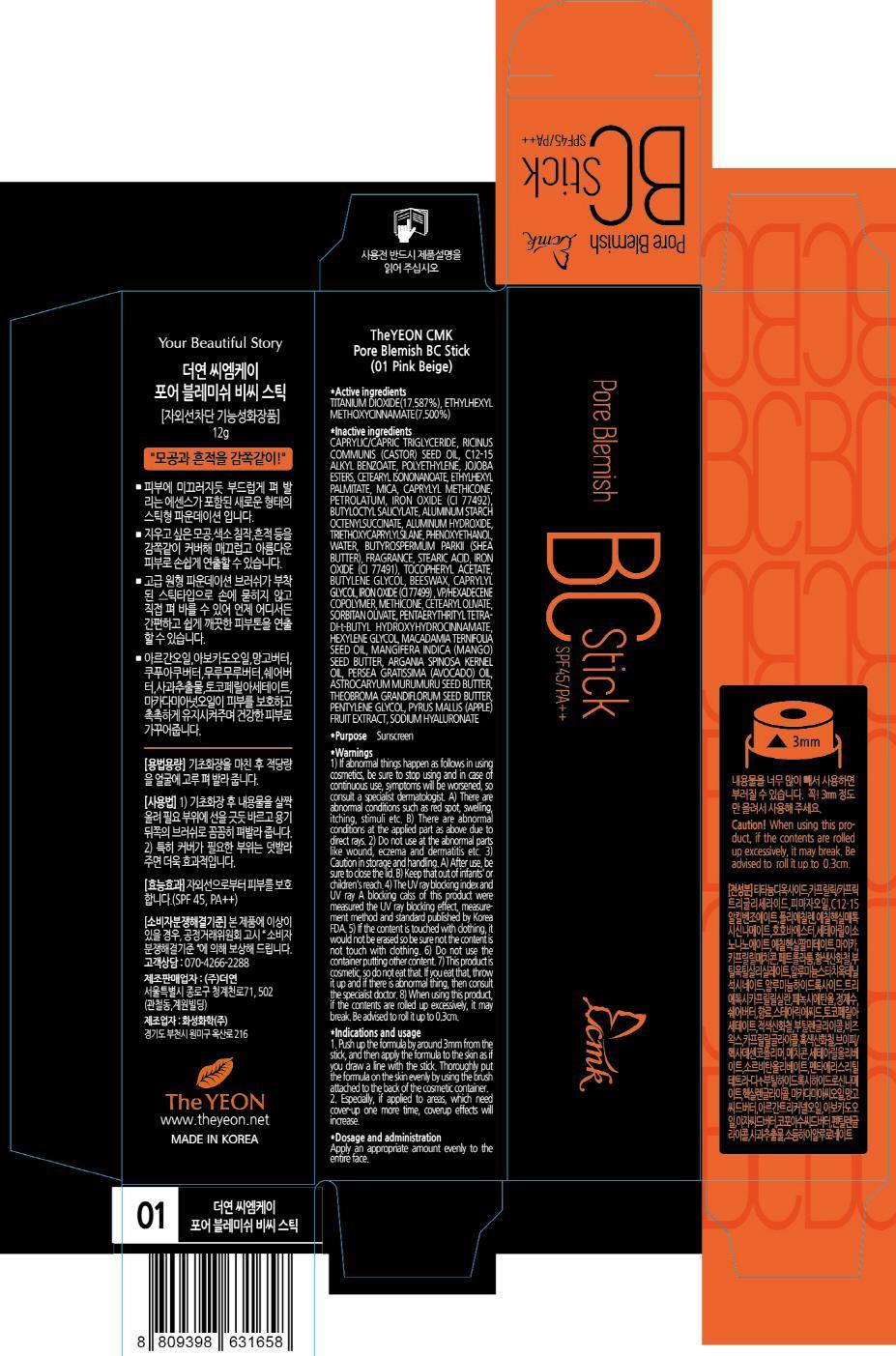 DRUG LABEL: THE YEON CMK PORE BLEMISH BC
NDC: 69154-010 | Form: CREAM
Manufacturer: The Yeon Co., Ltd.
Category: otc | Type: HUMAN OTC DRUG LABEL
Date: 20140820

ACTIVE INGREDIENTS: TITANIUM DIOXIDE 2.11 g/12 g; OCTINOXATE 0.90 g/12 g
INACTIVE INGREDIENTS: CETEARYL ISONONANOATE; ETHYLHEXYL PALMITATE

ACTIVE INGREDIENT

Active ingredients: TITANIUM DIOXIDE 17.587%, ETHYLHEXYL METHOXYCINNAMATE 7.500%

INACTIVE INGREDIENT

Inactive ingredients:
CAPRYLIC/CAPRIC TRIGLYCERIDE, RICINUS COMMUNIS (CASTOR) SEED OIL, C12-15 ALKYL BENZOATE, POLYETHYLENE, JOJOBA ESTERS, CETEARYL ISONONANOATE, ETHYLHEXYL PALMITATE, MICA, CAPRYLYL METHICONE, PETROLATUM, IRON OXIDE (CI 77492), BUTYLOCTYL SALICYLATE, ALUMINUM STARCH OCTENYLSUCCINATE, ALUMINUM HYDROXIDE, TRIETHOXYCAPRYLYLSILANE, PHENOXYETHANOL, WATER, BUTYROSPERMUM PARKII (SHEA BUTTER), FRAGRANCE, STEARIC ACID, IRON OXIDE (CI 77491), TOCOPHERYL ACETATE, BUTYLENE GLYCOL, BEESWAX, CAPRYLYL GLYCOL, IRON OXIDE (CI 77499), VP/HEXADECENE COPOLYMER, METHICONE, CETEARYL OLIVATE, SORBITAN OLIVATE, PENTAERYTHRITYL TETRA-DI-t-BUTYL HYDROXYHYDROCINNAMATE, HEXYLENE GLYCOL, MACADAMIA TERNIFOLIA SEED OIL, MANGIFERA INDICA (MANGO) SEED BUTTER, ARGANIA SPINOSA KERNEL OIL, PERSEA GRATISSIMA (AVOCADO) OIL, ASTROCARYUM MURUMURU SEED BUTTER,
THEOBROMA GRANDIFLORUM SEED BUTTER, PENTYLENE GLYCOL, PYRUS MALUS (APPLE) FRUIT EXTRACT, SODIUM HYALURONATE

PURPOSE

Purpose: Sunscreen

WARNINGS

1) If abnormal things happen as follows in using cosmetics, be sure to stop using and in case of continuous use, symptoms will be worsened, so consult a specialist dermatologist. A) There are abnormal conditions such as red spot, swelling, itching, stimuli etc. B) There are abnormal conditions at the applied part as above due to direct rays.
2) Do not use at the abnormal parts like wound, eczema and dermatitis etc.
3) Caution in storage and handling. A) After use, be sure to close the lid. B) Keep that out of infants' or children's reach.
4) The UV ray blocking index and UV ray A blocking calss of this product were measured the UV ray blocking effect, measurement method and standard published by Korea FDA.
5) If the content is touched with clothing, it would not be erased so be sure not the content is not touch with clothing.
6) Do not use the container putting other content.
7) This product is cosmetic, so do not eat that. If you eat that, throw it up and if there is abnormal thing, then consult the specialist doctor.
8) When using this product,if the contents are rolled up excessively, it may break. Be advised to roll it up to 0.3cm.

KEEP OUT OF REACH OF CHILDREN

Keep that out of infants' or children's reach.

Indications and usage

1. Push up the formula by around 3mm from the stick, and then apply the formula to the skin as if you draw a line with the stick. Thoroughly put the formula on the skin evenly by using the brush attached to the back of the cosmetic container.
2. Especially, if applied to areas, which need cover-up one more time, coverup effects will increase.

Dosage and administration

Apply an appropriate amount evenly to the entire face.